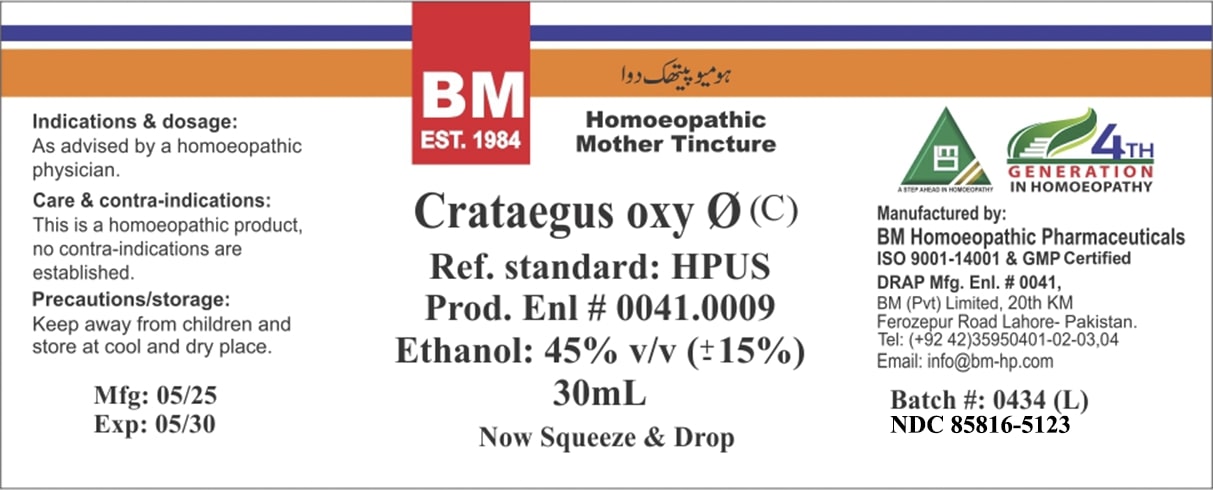 DRUG LABEL: BM Crataegus Oxy
NDC: 85816-5123 | Form: TINCTURE
Manufacturer: BM Private Limited
Category: homeopathic | Type: HUMAN OTC DRUG LABEL
Date: 20250701

ACTIVE INGREDIENTS: CRATAEGUS FRUIT 1 [hp_X]/1 mL
INACTIVE INGREDIENTS: WATER 0.3 mL/1 mL; ALCOHOL 0.7 mL/1 mL

BM Crataegus Oxy Ø

ACTIVE INGREDIENT

CRATAEGUS OXYACANTHA

INACTIVE INGREDIENT

ALCOHOL, WATER

Indications & dosage: As advised by a homoeopathic physician.

Indications & dosage: As advised by a homoeopathic physician.

PURPOSE

Indications & dosage: As advised by a homoeopathic physician.

CONTRAINDICATIONS

Care & contra-indications: This is a homoeopathic product, no contra-indications are established.

WARNINGS

Precautions/storage: Keep away from children and store at cool and dry place.

KEEP OUT OF REACH OF CHILDREN

Precautions/storage: Keep away from children and store at cool and dry place.

STORAGE AND HANDLING

Precautions/storage: Keep away from children and store at cool and dry place.

Entire package label